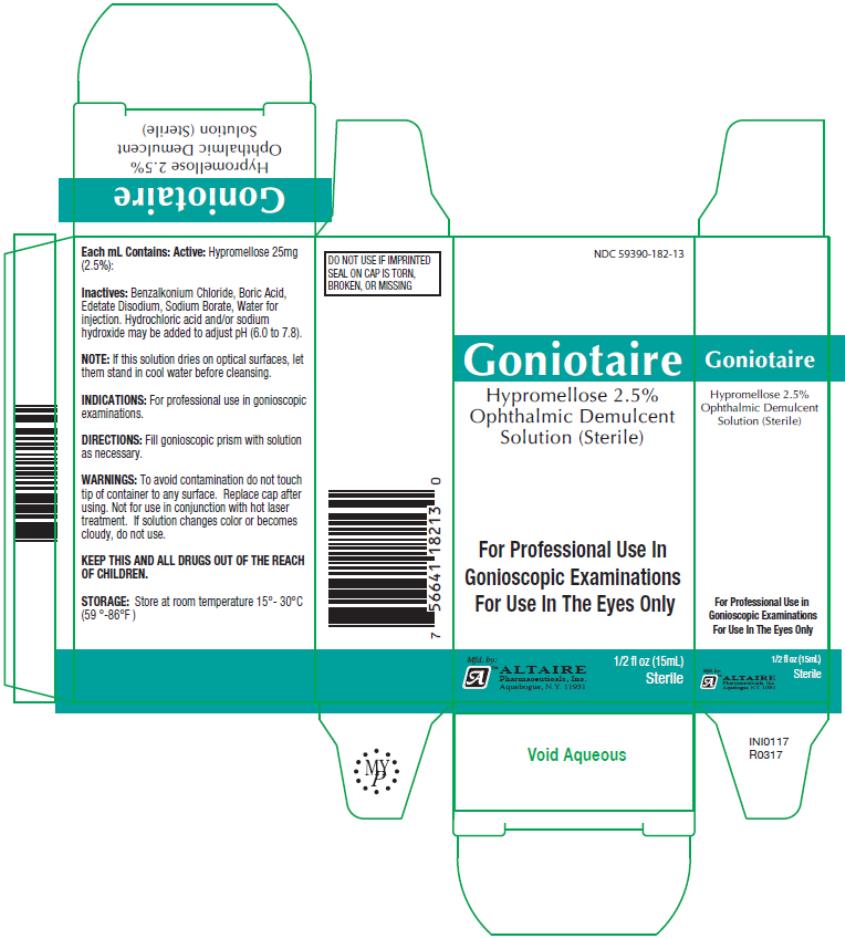 DRUG LABEL: Goniotaire
NDC: 59390-182 | Form: SOLUTION
Manufacturer: Altaire Pharmaceuticals Inc.
Category: prescription | Type: HUMAN PRESCRIPTION DRUG LABEL
Date: 20221028

ACTIVE INGREDIENTS: HYPROMELLOSE 2906 (4000 MPA.S) 25 mg/1 mL
INACTIVE INGREDIENTS: BENZALKONIUM CHLORIDE; BORIC ACID; EDETATE DISODIUM; SODIUM BORATE; WATER

Goniotaire

Altaire

Goniotaire

Hypromellose 2.5% Ophthalmic

Demulcent Solution

15mL

NDC 59390-182-13

Drug Facts

Each m L Contains:

Active:

Hypromellose 25mg (2.5%):

Inactives:

Benzalkonium Chloride, Boric Acid, Edetate Disodium, Sodium Borate, Water for injection. Hydrochloric Acid and/or sodium hydroxide may be added to adjust pH (6.0 to 7.8).

NOTE: If this solution dries on optical surfaces, let them stand in cool water before cleansing.

INDICATIONS:

For professional use in gonioscopic examinations.

DIRECTIONS:

Fill gonioscopic prism with solution as necessary.

WARNINGS:

To avoid contamination do not touch tip of container to any surface. Replace cap after using. Not for use in conjunction with hot laser treatment. If solution changes color or becomes cloudy, do not use.

STORAGE:

Store at room temperature 15°- 30°C (59°- 86°F).

PRINCIPAL DISPLAY PANEL

NDC 59390-182-13
Goniotaire
Hypromellose 2.5%
Ophthalmic Demulcent
Solution (Sterile)
½ fl oz (15mL)
sterile